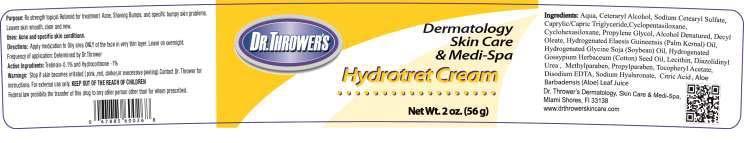 DRUG LABEL: DR. THROWERS HYDROTET
NDC: 69299-102 | Form: CREAM
Manufacturer: DR. THROWER'S SKINCARE, INC.
Category: prescription | Type: HUMAN PRESCRIPTION DRUG LABEL
Date: 20150522

ACTIVE INGREDIENTS: TRETINOIN 0.05 g/100 g; HYDROCORTISONE 1 g/100 g
INACTIVE INGREDIENTS: WATER; CETOSTEARYL ALCOHOL; SODIUM CETOSTEARYL SULFATE; MEDIUM-CHAIN TRIGLYCERIDES; CYCLOMETHICONE 5; CYCLOMETHICONE 6; PROPYLENE GLYCOL; ALCOHOL; DECYL OLEATE; HYDROGENATED PALM KERNEL OIL; HYDROGENATED SOYBEAN OIL; HYDROGENATED COTTONSEED OIL; LECITHIN, SOYBEAN; DIAZOLIDINYL UREA; METHYLPARABEN; PROPYLPARABEN; .ALPHA.-TOCOPHEROL ACETATE; EDETATE DISODIUM; HYALURONATE SODIUM; ANHYDROUS CITRIC ACID; ALOE VERA LEAF

DIRECTIONS:

APPLY MEDICATION TO OILY AREA ONLY OF THE FACE IN VERY THIN LAYER. LEAVE ON OVERNIGHT.

PURPOSE:

RX STRENGTH TOPICAL RETINOID FOR TREATMENT OF ACNE, SHAVING BUMPS, AND SPECIFIC BUMPY SKIN PROBLEMS. LEAVES SKIN SMOOTH, CLEAR AND NEW.

uSES: ACNE AND SPECIFIC SKIN CONDITIONS.

INGREDIENTS:

Aqua, Ceteraryl Alcohol, Sodium Cetearyl Sulfate, Caprylic/Capric Triglyceride,Cyclopentasiloxane, Cyclohexasiloxane, Propylene Glycol, Alcohol Denatured, Decyl Oleate, Hydrogenated Elaesis Guineensis (Palm Kernal) Oil, Hydrogenated Glycine Soja (Soybean) Oil, Hydrogenated Gossypium Herbaceum (Cotton) Seed Oil, Lecithin, Diazolidinyl Urea , Methylparaben, Propylparaben, Tocopheryl Acetate, Disodium EDTA, Sodium Hyaluronate, Citric Acid , Aloe Barbadensis (Aloe) Leaf Juice

WARNINGS

STOP USE IF SKIN BECOMES IRRITATED (PINK, RED DARKER, OR EXCESSIVE PEELING). cONTACT DR. THROWER FOR INSTRUCTIONS. FOR EXTERNAL USE ONLY. KEEP OUT OF REACH OF CHILDREN. FEDERAL LAW PROHIBITS THE TRANSFER OF THIS DRUG TO ANY OTHER PERSON OTHER THAN FOR WHOM IT IS PRESCRIBED.